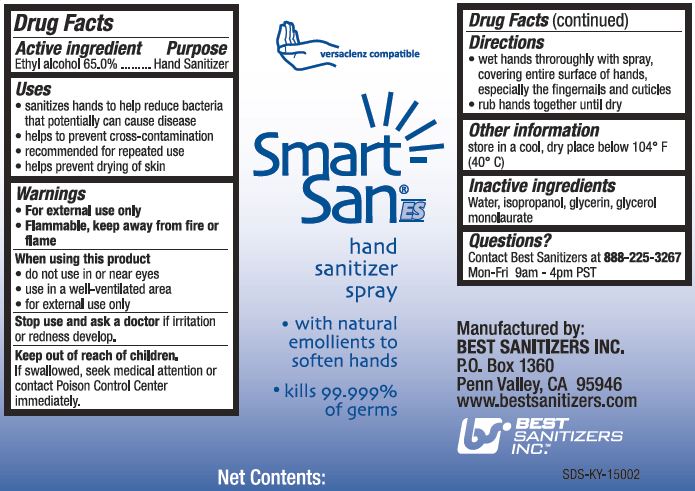 DRUG LABEL: SMART SAN HAND SANITIZER
NDC: 59900-124 | Form: LIQUID
Manufacturer: Best Sanitizers, Inc.
Category: otc | Type: HUMAN OTC DRUG LABEL
Date: 20241205

ACTIVE INGREDIENTS: ALCOHOL 65 mm/100 mL
INACTIVE INGREDIENTS: WATER; ISOPROPYL ALCOHOL; GLYCERIN; GLYCERYL LAURATE

Drug Facts - 59900-124

Active ingredient

Ethyl alcohol 65.0%

Purpose

Hand Sanitizer

Uses

- sanitizes hands to help reduce bacteria that potentially can cause disease

- helps to prevent cross-contamination

- recommended for repeated use

- helps prevent drying of skin

Warnings

- For external use only

- Flammable, keep away from fire or flame

When using this product

- do not use in or near eyes

- use in a well-ventilated area

- for external use only

Stop use and ask a doctorif irritation or redness develop.

Keep out of reach of children.

If swallowed, seek medical attention or contact Poison Control Center immediately.

Directions

- wet hands thoroughly with spray, covering entire surface of hands, especially the fingernails and cuticles

- rub hands together until dry

Other information

store in a cool, dry place below 104oF (40oC)

Inactive ingredients

Water, isopropanol, glycerin,glycerol monolarurate

Questions?

Contact Best Sanitizers at 888-225-3267Mon-Fri 9am - 4 pm PST

PACKAGE LABEL

versaclenz compatible

Smart

San

hand

sanitizer

spray

with natural

emollients to

soften hands

kills 99.999%

of germs

Net Contents: